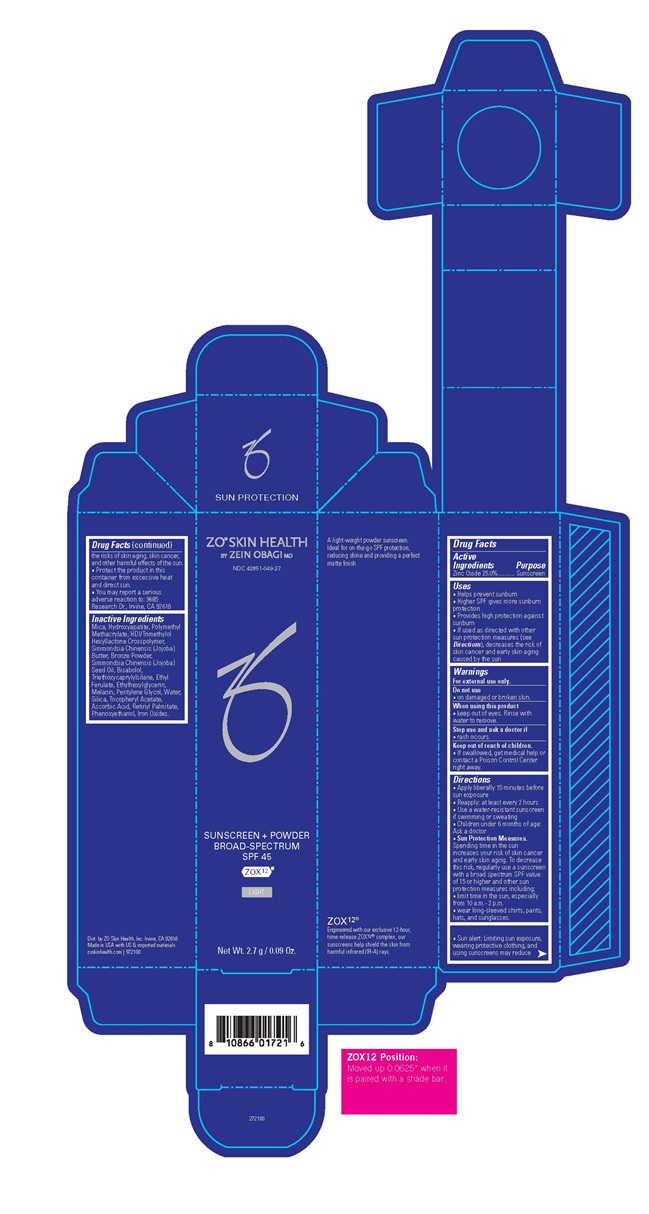 DRUG LABEL: ZO Skin Health Sunscreen Plus Powder Broad-Spectrum SPF 45 (Light)
NDC: 42851-049 | Form: POWDER
Manufacturer: ZO Skin Health, Inc.
Category: otc | Type: HUMAN OTC DRUG LABEL
Date: 20241227

ACTIVE INGREDIENTS: ZINC OXIDE 0.675 mg/1 g
INACTIVE INGREDIENTS: TRIBASIC CALCIUM PHOSPHATE; POLY(METHYL METHACRYLATE; 450000 MW); COPPER; TRIETHOXYCAPRYLYLSILANE; WATER; MICA; ETHYLHEXYLGLYCERIN; HEXAMETHYLENE DIISOCYANATE/TRIMETHYLOL HEXYLLACTONE CROSSPOLYMER; JOJOBA BUTTER; JOJOBA OIL; LEVOMENOL; ETHYL FERULATE; ASCORBIC ACID; FERRIC OXIDE RED; PENTYLENE GLYCOL; .ALPHA.-TOCOPHEROL ACETATE; VITAMIN A PALMITATE; PHENOXYETHANOL; SILICON DIOXIDE

ZO ® Skin Health Sunscreen + Powder Broad-Spectrum SPF 45 (Light)
National Drug Code 42851-049-27

Drug Facts

Active Ingredients

Active Ingredient | Purpose
Zinc Oxide 25.0% | Sunscreen

Purpose Sunscreen

Uses

- Helps prevent sunburn
- Higher SPF gives more sunburn protection
- Provides high protection against sunburn
- If used as directed with other sun protection measures (see Directions), decreases the risk of skin cancer and early skin aging caused by the sun

Warnings

For external use only.

Do not use

- on damaged or broken skin.

When using this product

- keep out of eyes. Rinse with water to remove.

Stop use and ask a doctor if

- rash occurs.

ASK DOCTOR

- If swallowed, get medical help or contact a Poison Control Center right away.

Directions
■ Apply liberally 15 minutes before sun exposure
■ Reapply: at least every 2 hours
■ Use a water-resistant sunscreen if swimming or sweating
■ Children under 6 months of age: Ask a doctor
■ Sun Protection Measures.
Spending time in the sun increases your risk of skin cancer
and early skin aging. To decrease this risk, regularly use a
sunscreen with a broad spectrum SPF value of 15 or higher and
other sun protection measures including:
■ Limit time in the sun, especially from 10 a.m. – 2 p.m.
■ Wear long-sleeved shirts, pants, hats, and sunglasses.
■ Sun alert: Limiting sun exposure, wearing protective clothing,
and using sunscreens may reduce the risks of skin aging, skin cancer,
and other harmful effects of the sun.
■ Protect the product in this container from excessive
heat and direct sun.
■ You may report a serious adverse reaction
to: 9685 Research Dr., Irvine, CA 92618

Other Information

- Sun alert: Limiting sun exposure, wearing protective clothing, and using sunscreens may reduce the risks of skin aging, skin cancer, and other harmful effects of the sun.
- Protect the product in this container from excessive heat and direct sun.
- You may report a serious adverse reaction to: 9685 Research Dr., Irvine, CA 92618

Inactive Ingredients

Mica, Hydroxyapatite, Polymethyl Methacrylate, HDI/Trimethylol Hexyllactone Crosspolymer, Simmondsia Chinensis (Jojoba) Butter, Bronze Powder, Simmondsia Chinensis (Jojoba) Seed Oil, Bisabolol, Triethoxycaprylylsilane, Ethyl Ferulate, Ethylhexylglycerin, Melanin, Pentylene Glycol, Water, Silica, Tocopheryl Acetate, Ascorbic Acid, Retinyl Palmitate, Phenoxyethanol, Iron Oxides.

Dist. by ZO Skin Health, Inc. Irvine, CA 92618

Made in USA with US & imported materials

Principal Display Panel

ZO® SKIN HEALTH

BY ZEIN OBAGI MD

NDC 42851-049-27

SUNSCREEN + POWDR BROAD-SPECTRUM SPF 45

ZOX12™

LIGHT

Net Wt. 2.7 g / 0.09 Oz.

res